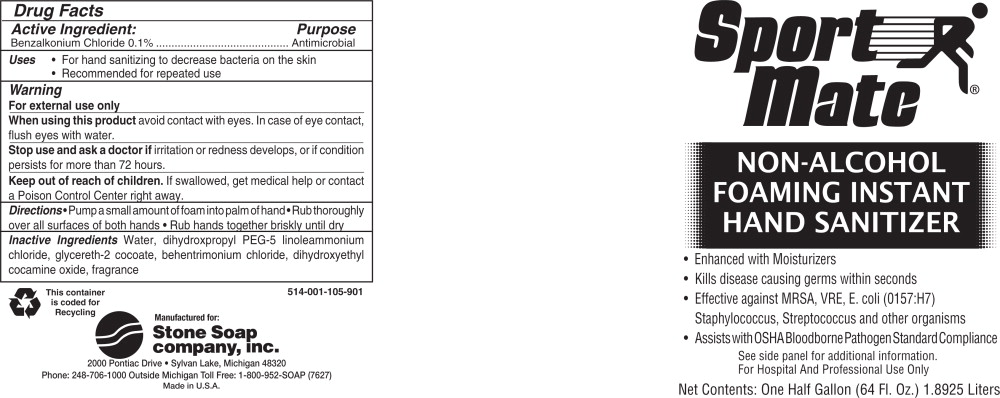 DRUG LABEL: Sport Mate Non-Alcohol Foaming Instant Hand Sanitizer
NDC: 62065-514 | Form: SOLUTION
Manufacturer: Stone Soap Company, Inc.
Category: otc | Type: HUMAN OTC DRUG LABEL
Date: 20100402

ACTIVE INGREDIENTS: benzalkonium chloride 1 g/1000 mL
INACTIVE INGREDIENTS: water; dihydroxypropyl PEG-5 linoleammonium chloride; glycereth-2 cocoate; behentrimonium chloride; dihydroxyethyl cocamine oxide

Drug Facts

Active Ingredient:

Benzalkonium Chloride 0.1%

Purpose

Antimicrobial

Uses

- For hand sanitizing to decrease bacteria on the skin
- Recommended for repeated use

Warning

For external use only

When using this product avoid contact with eyes. In case of eye contact, flush eyes with water.

Stop use and ask a doctor if irritation or redness develops, or if condition persists for more than 72 hours.

Keep out of reach of children. If swallowed, get medical help or contact a Poison Control Center right away.

Directions

- Pump a small amount of foam into palm of hand
- Rub thoroughly over all surfaces of both hands
- Rub hands together briskly until dry

Inactive Ingredients

Water, dihydroxpropyl PEG-5 linoleammonium chloride, glycereth-2 cocoate, behentrimonium chloride, dihydroxyethyl cocamine oxide, fragrance

Principal Display Panel

Sport Mate

Non-Alcohol Foaming Instant Hand Sanitizer

- Enhanced with Moisturizers
- Kills disease causing germs within seconds
- Effective against MRSA, VRE, E. coli (0157:H7) Staphylococcus, Streptococcus and other organisms
- Assists with OSHA Bloodborne Pathogen Standard Compliance

See side panel for additional information.

For Hospital and Professional Use Only